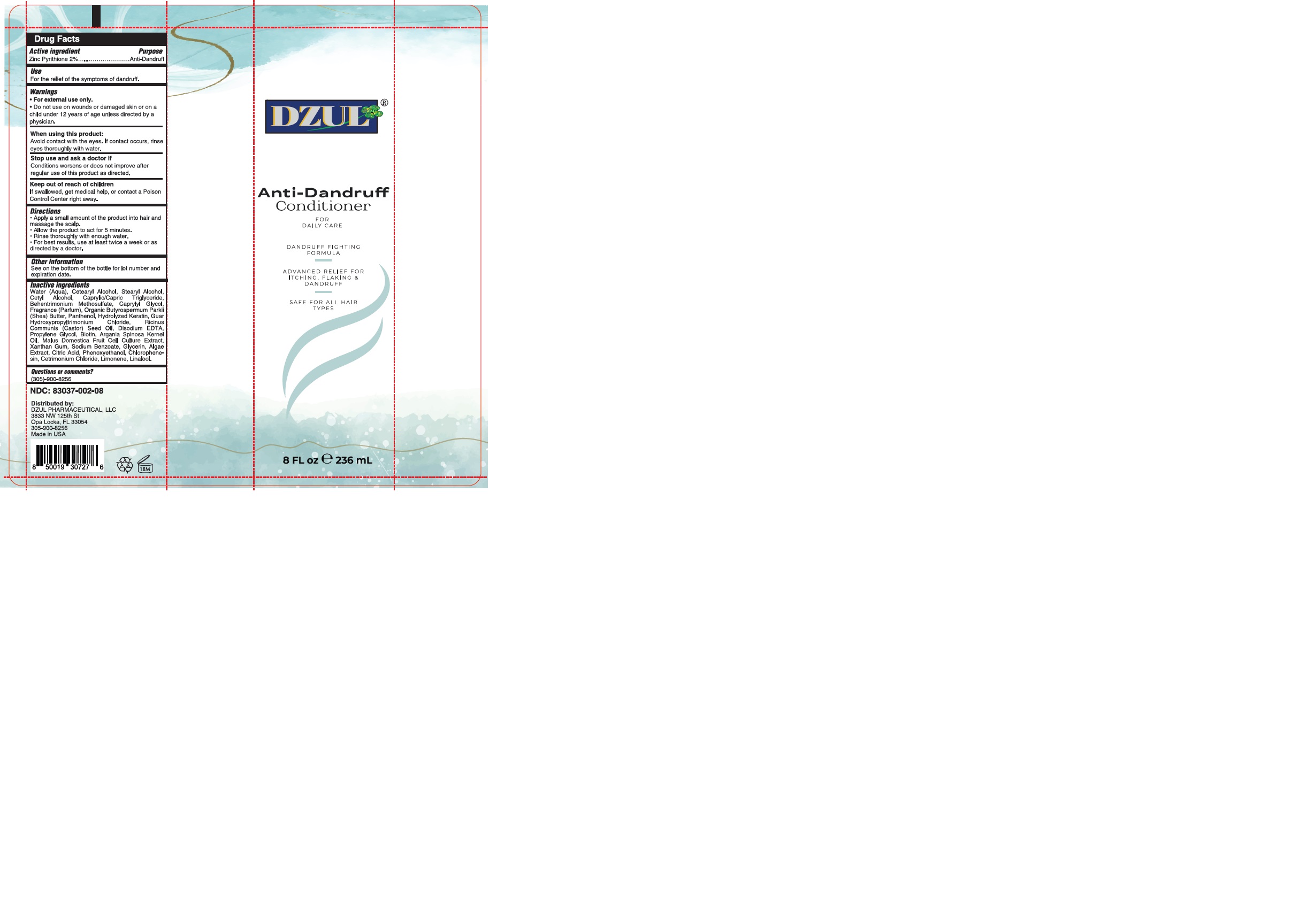 DRUG LABEL: DZUL ANTI-DANDRUFF CONDITIONER
NDC: 83037-002 | Form: CREAM
Manufacturer: Caball Sales, Inc.
Category: otc | Type: HUMAN OTC DRUG LABEL
Date: 20241122

ACTIVE INGREDIENTS: PYRITHIONE ZINC 2 g/100 mL
INACTIVE INGREDIENTS: PROPYLENE GLYCOL; ARGANIA SPINOSA WHOLE; XANTHAN GUM; CAPRYLYL GLYCOL; PHENOXYETHANOL; PANTHENOL; BIOTIN; WATER; SODIUM BENZOATE; MALUS DOMESTICA WHOLE; EDETATE DISODIUM; ANHYDROUS CITRIC ACID; CETOSTEARYL ALCOHOL; LIMONENE, (+)-; ASCOPHYLLUM NODOSUM; GUAR HYDROXYPROPYLTRIMONIUM CHLORIDE (1.7 SUBSTITUENTS PER SACCHARIDE); CASTOR OIL; GLYCERIN; CHLORPHENESIN; CETRIMONIUM CHLORIDE; CETYL ALCOHOL; SHEA BUTTER; STEARYL ALCOHOL; MEDIUM-CHAIN TRIGLYCERIDES; BEHENTRIMONIUM METHOSULFATE; LINALOOL, (+/-)-

83037-002-08

ACTIVE INGREDIENT

Pyrithione Zinc 2%

PURPOSE

Anti-Dandruff

INDICATIONS AND USAGE

For the relief of the symptoms of dandruff

WARNINGS

For external use only.

Do not use on wounds or damaged skin or on a child under 12 years of age unless directed by a physician

When using this product do not get into eyes. If contact occurs, rinse eyes thoroughly with water.

Stop use and ask a doctor if condition worsens or does not improve after regular use as directed.

KEEP OUT OF REACH OF CHILDREN

If swallowed, get medical help or contact a Poison Control Center right away

DOSAGE AND ADMINISTRATION

Apply a small amount quantity of the product into hair and massage the scalp.
Allow the product to act for 5 minutes.
Rinse thoroughly with enough water.

For best results, use at least twice a week or as directed by a doctor.

OTHER SAFETY INFORMATION

See on the bottom of the bottle for lot number and expiration date.

INACTIVE INGREDIENT

Water (Aqua), Cetearyl Alcohol, Stearyl Alcohol, Cetyl Alcohol, Caprylic/Capric Triglyceride, Behentrimonium Methosulfate, Caprylyl Glycol, Fragrance (Parfum), Organic Butyrospermum Parkii (Shea) Butter, Panthenol, Hydrolyzed Keratin, Guar Hydroxypropyltrimonium Chloride, Ricinus Communis (Castor) Seed Oil, Disodium EDTA, Propylene Glycol, Biotin, Argania Spinosa Kernel Oil, Malus Domestica Fruit Cell Culture Extract, Xanthan Gum, Sodium Benzoate, Glycerin, Algae Extract, Citric Acid, Phenoxyethanol, Chlorophenesin, Cetrimonium Chloride, Limonene, Linalool.

Questions or comments?

Call (305)-900-8256